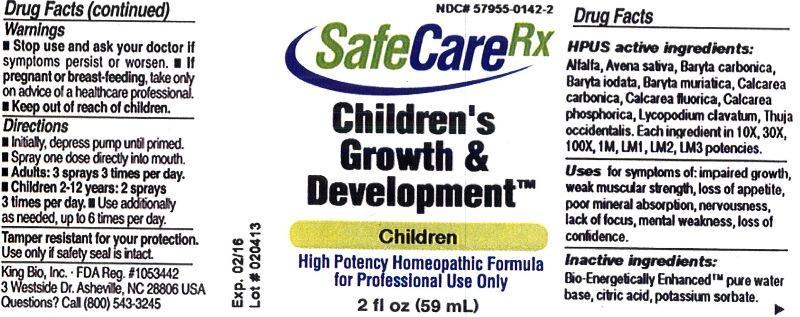 DRUG LABEL: Childrens Growth and Development
NDC: 57955-0142 | Form: LIQUID
Manufacturer: King Bio Inc.
Category: homeopathic | Type: HUMAN PRESCRIPTION DRUG LABEL
Date: 20130228

ACTIVE INGREDIENTS: ALFALFA 10 [hp_X]/59 mL; AVENA SATIVA FLOWERING TOP 10 [hp_X]/59 mL; BARIUM CARBONATE 10 [hp_X]/59 mL; BARIUM IODIDE 10 [hp_X]/59 mL; BARIUM CHLORIDE DIHYDRATE 10 [hp_X]/59 mL; OYSTER SHELL CALCIUM CARBONATE, CRUDE 10 [hp_X]/59 mL; CALCIUM FLUORIDE 10 [hp_X]/59 mL; TRIBASIC CALCIUM PHOSPHATE 10 [hp_X]/59 mL; LYCOPODIUM CLAVATUM SPORE 10 [hp_X]/59 mL; THUJA OCCIDENTALIS LEAFY TWIG 10 [hp_X]/59 mL
INACTIVE INGREDIENTS: WATER; CITRIC ACID MONOHYDRATE; POTASSIUM SORBATE

Childrens Growth and Development

Warnings

- Stop use and ask your doctor if symptoms persist or worsen.
- If pregnant or breast-feeding, take only on advice of a healthcare professional.
- Keep out of reach of children.

Tamper resistant for your protection. Use only if safety seal is intact.

Keep out of reach of children.

Directions

- Initially, depress pump until primed.
- Spray one dose directly into mouth.
- Adults: 3 sprays 3 times per day.
- Children 2-12 years: 2 sprays 3 times per day
- Use additionally as needed, up to 6 times per day.

HPUS active ingredients

Alfalfa, Avena sativa, Baryta carbonica, Baryta iodata, Baryta muriatica, Calcarea carbonica, Calcarea fluorica, Calcarea phosphorica, Lycopodium clavatum and Thuja occidentalis.

Each ingredient in 10X, 30X, 100X, 1M, LM1, LM2, LM3 potencies.

Indications and Usage

Uses for symptoms of: impaired growth, weak muscular strength, loss of appetite, poor mineral absorption, nervousness, lack of focus, mental weakness, loss of confidence.

Inactive ingredients

Bio-Energetically Enhanced™ pure water base, citric acid and potassium sorbate

Purpose

Uses for symptoms of:

- impaired growth
- weak muscular strength
- loss of appetite
- poor mineral absorption
- nervousness
- lack of focus
- mental weakness
- loss of confidence